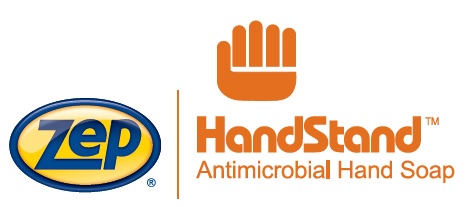 DRUG LABEL: Zep Handstand Antimicrobial
NDC: 66949-127 | Form: LIQUID
Manufacturer: Zep Inc.
Category: otc | Type: HUMAN OTC DRUG LABEL
Date: 20251226

ACTIVE INGREDIENTS: BENZALKONIUM CHLORIDE 0.13 g/100 mL
INACTIVE INGREDIENTS: SODIUM LAURIMINODIPROPIONATE; LAURAMINE OXIDE; SORBITOL; COCO MONOETHANOLAMIDE; ANHYDROUS CITRIC ACID; METHYLCHLOROISOTHIAZOLINONE; D&C RED NO. 33; WATER; CETRIMONIUM CHLORIDE; SODIUM CHLORIDE; PEG-120 METHYL GLUCOSE DIOLEATE; EDETATE DISODIUM ANHYDROUS; FD&C YELLOW NO. 5; METHYLISOTHIAZOLINONE

66949-127 / U429 Handstand Antimicrobial

Active ingredient

Benzalkonium Chloride 0.13%

Purpose

Antibacterial handwashing

Uses

Handwash to help decrease bacteria on the skin.

Warnings

For external use only.

Do not use in the eyes. In case of eye contact, immediately flush with water.

Stop use and ask a doctor if irritation or rash appears and lasts.

Keep out of reach of children. If swallow, get medical help or contact a Poison Control Center right away.

Directions

- Apply a small amount, covering hands with product for 30 seconds. Add water, lather and rinse.
- Children under 6 years of age should be supervised when using this product.

Inactive Ingredients

Water, Cetrimonium Chloride, Sodium Chloride, Lauramine Oxide, Sorbitol, Disodium EDTA, Cocamide MEA, PEG-120 Methyl Glucose Dioleate, Sodium Lauriminodipropionate, Citric Acid, Fragrance, Methylisothiazolinone, Methylchloroisothiazolinone, Yellow 5, Red 33

QUESTIONS

1-877-I-BUY-ZEP/1-877-428-9937